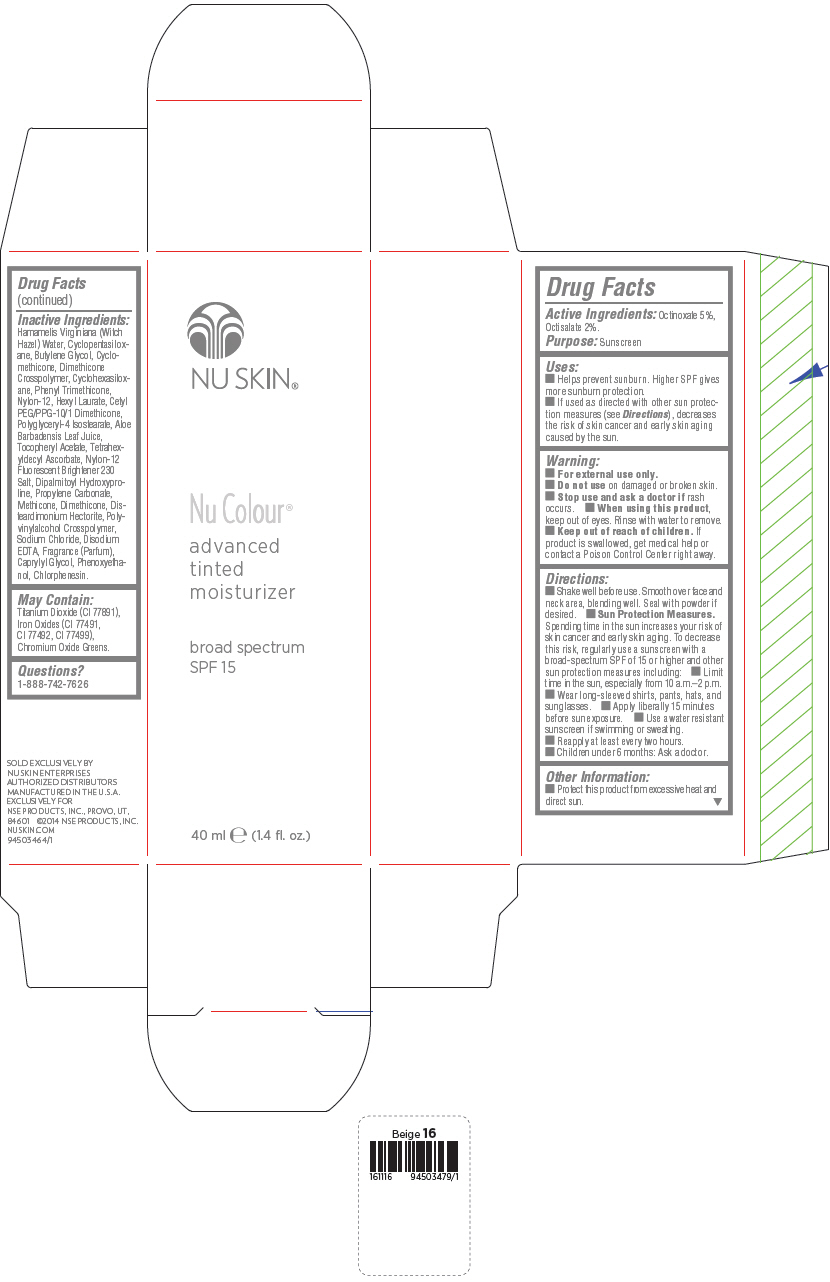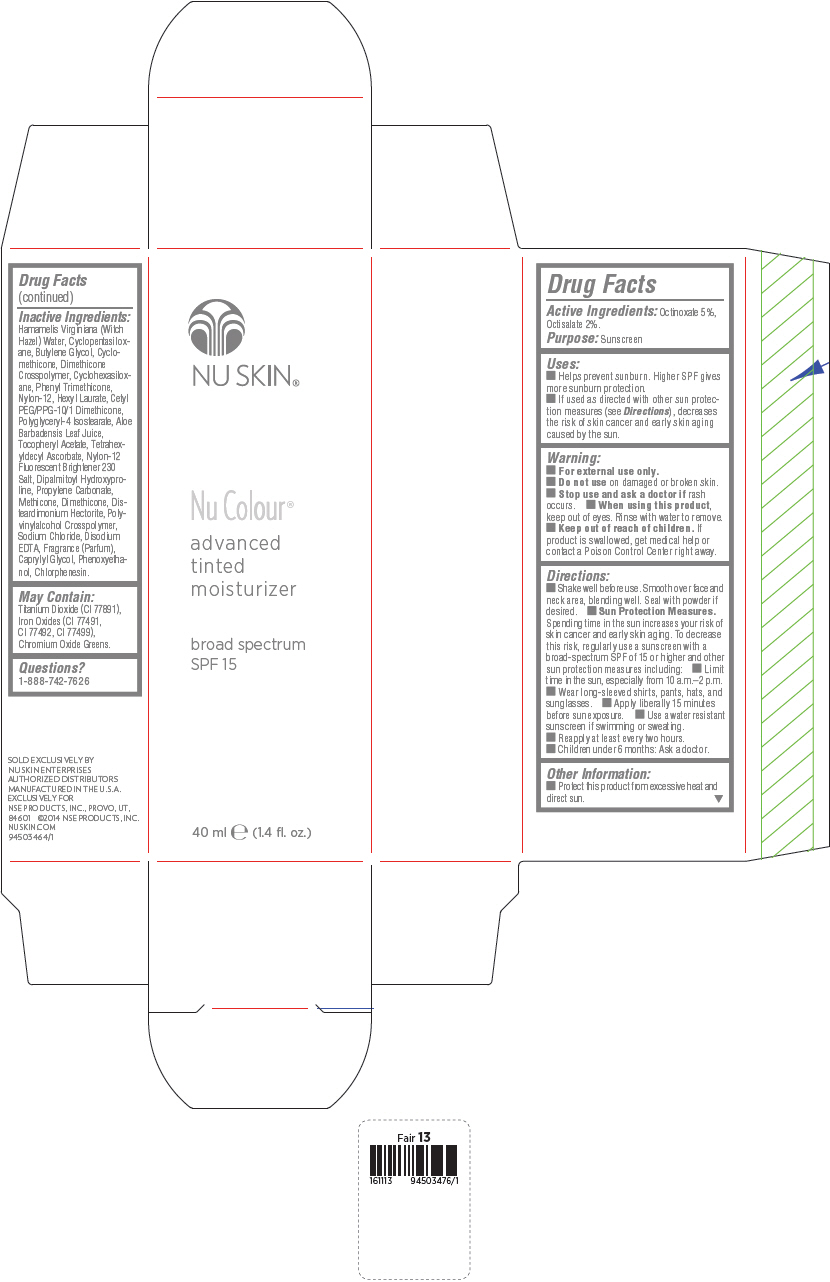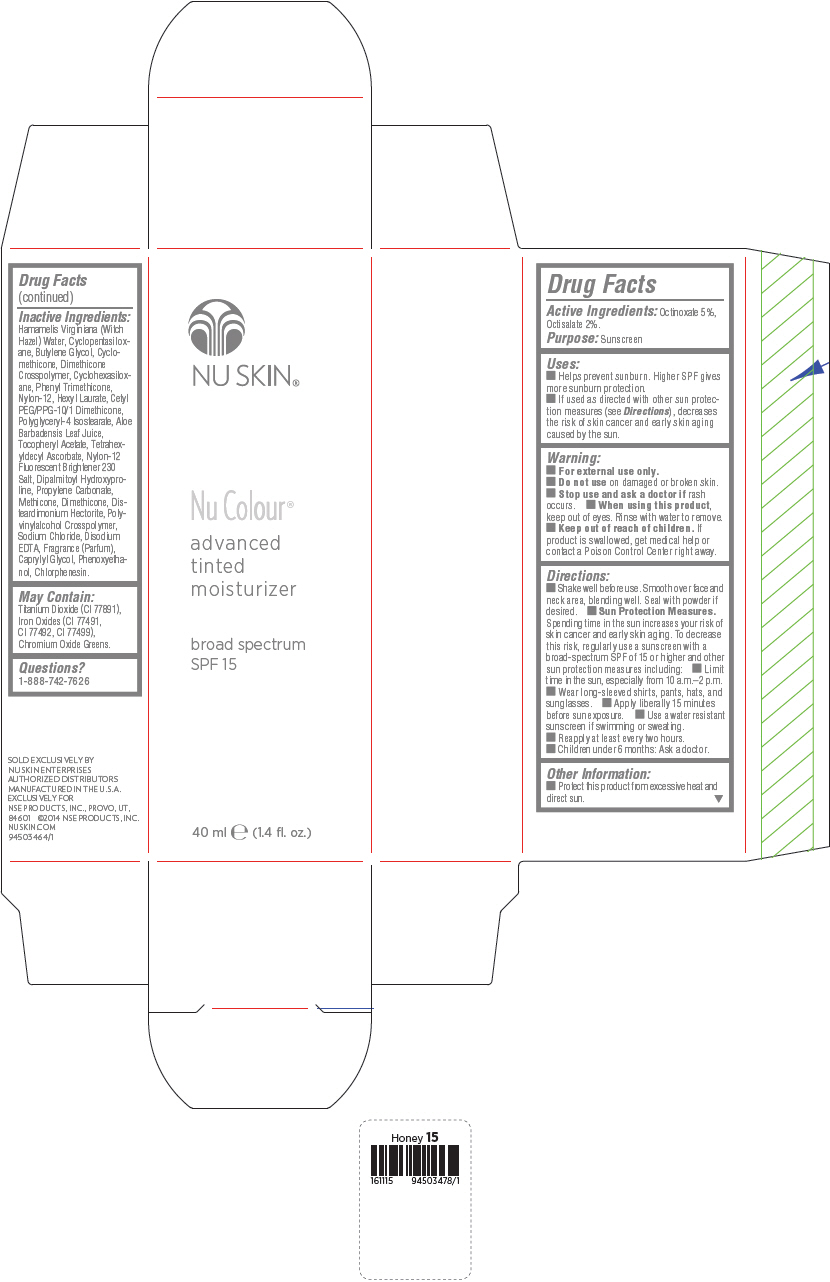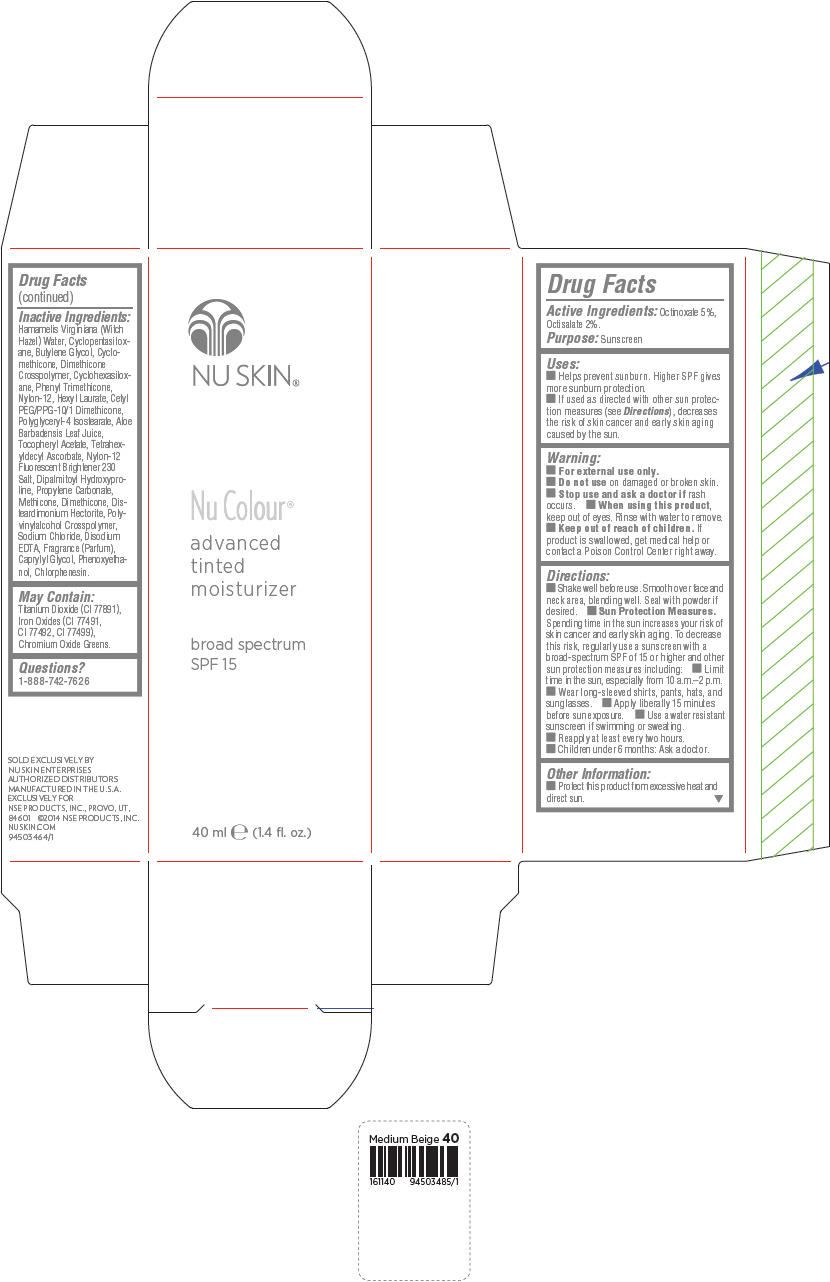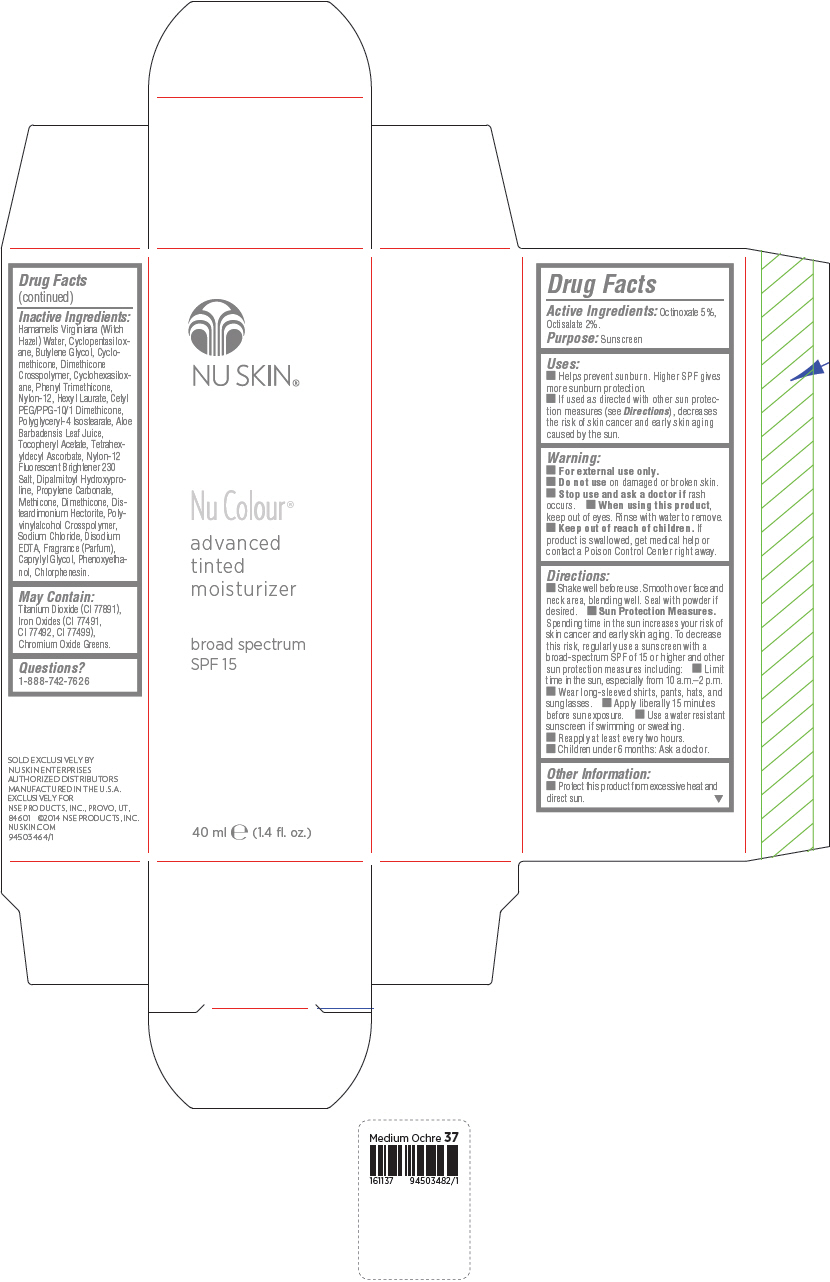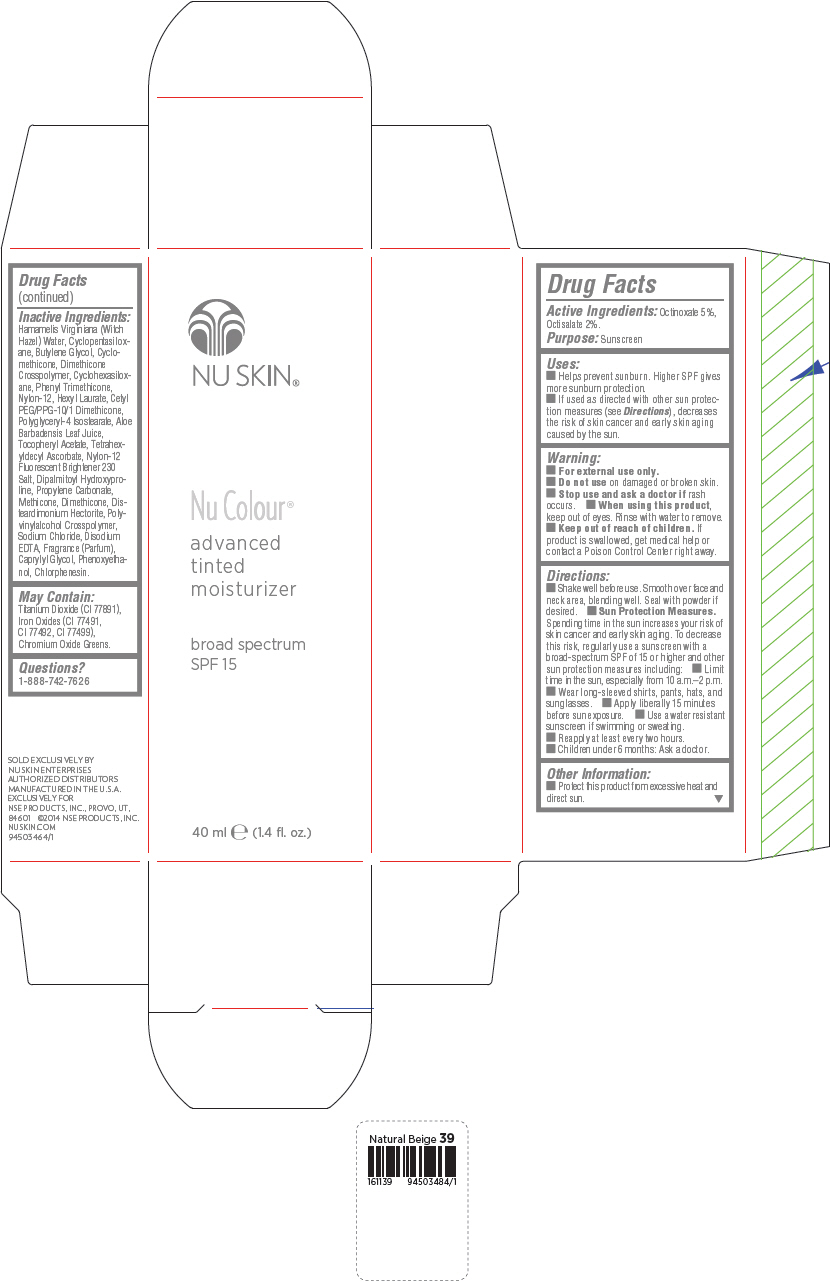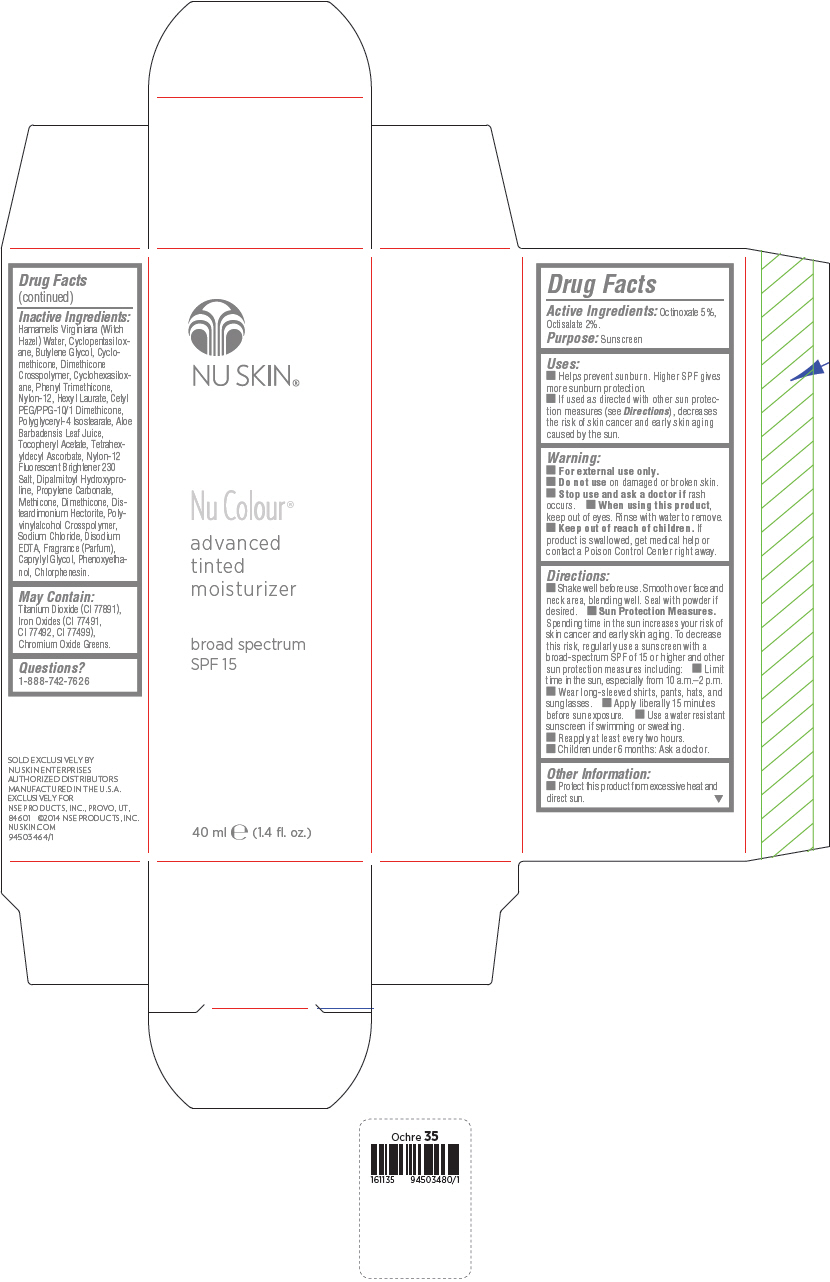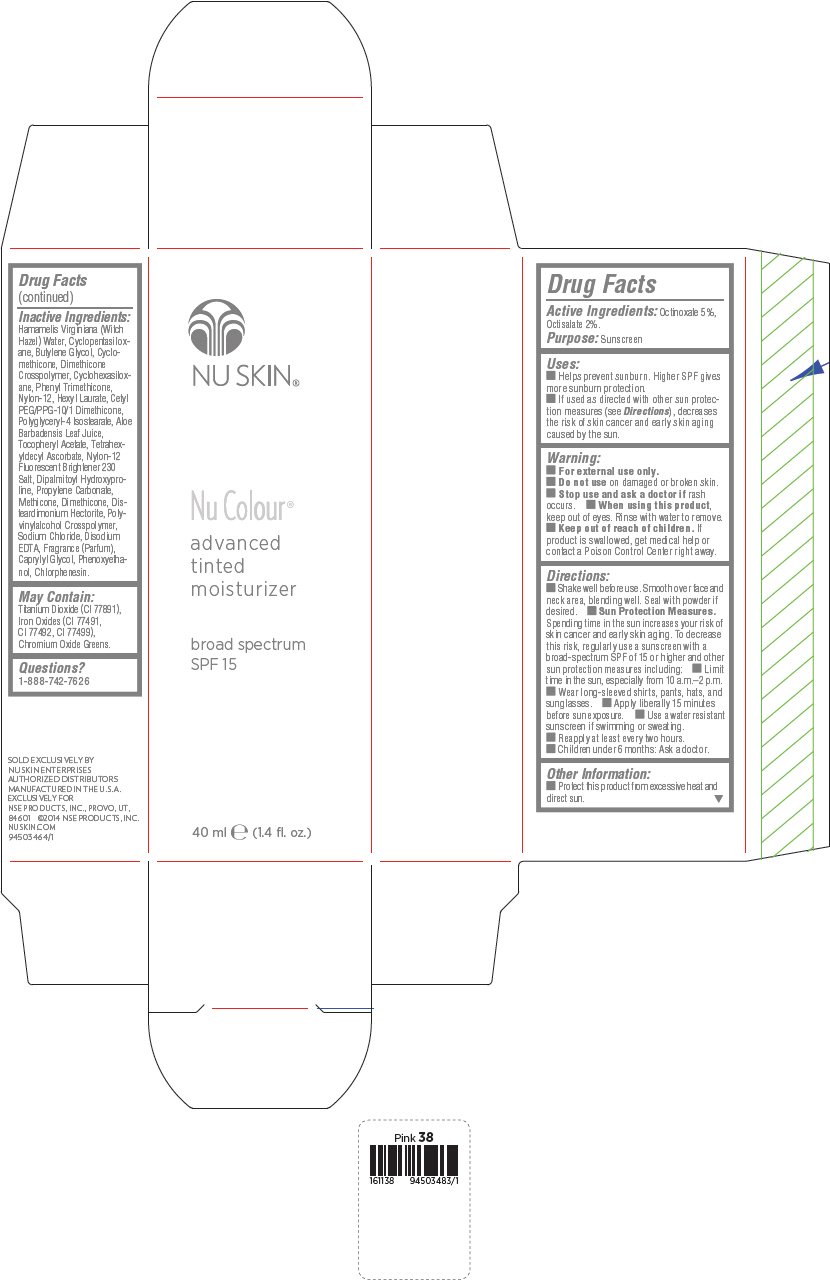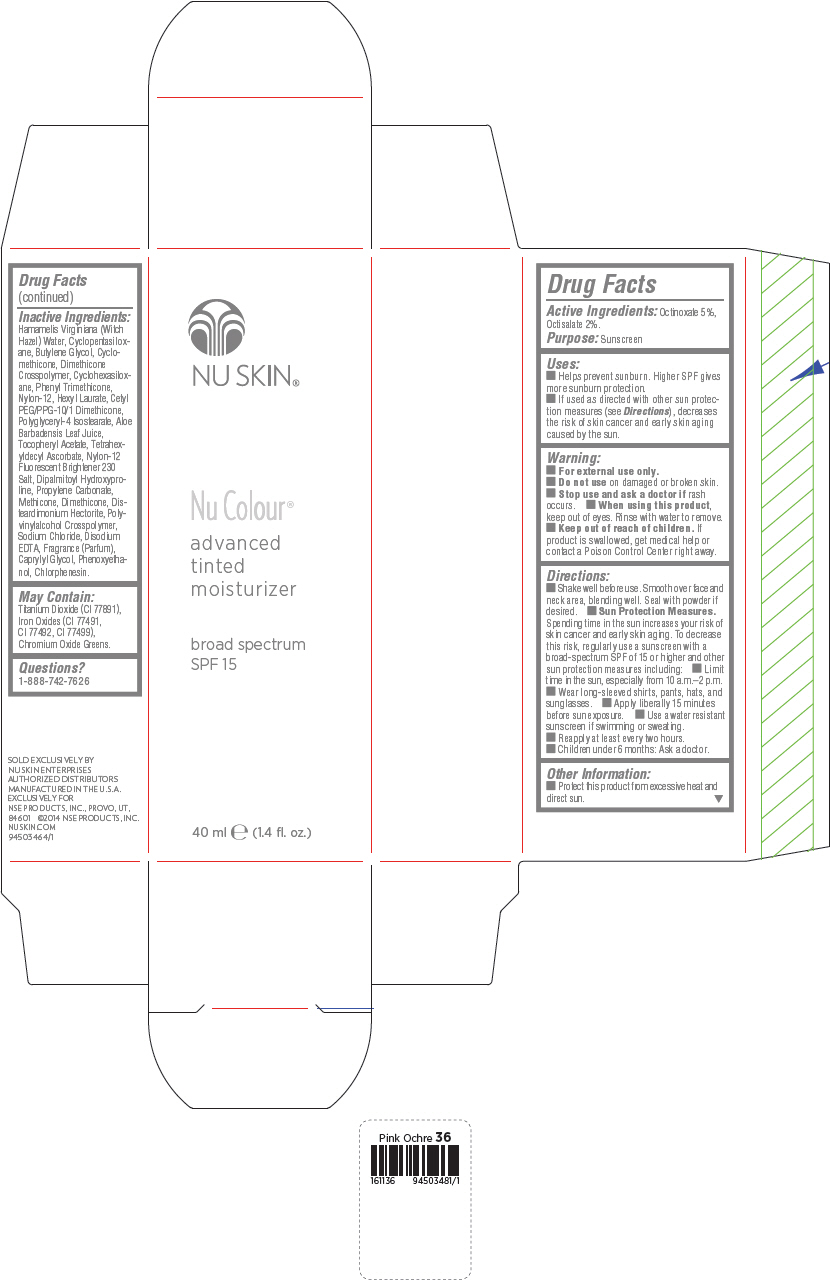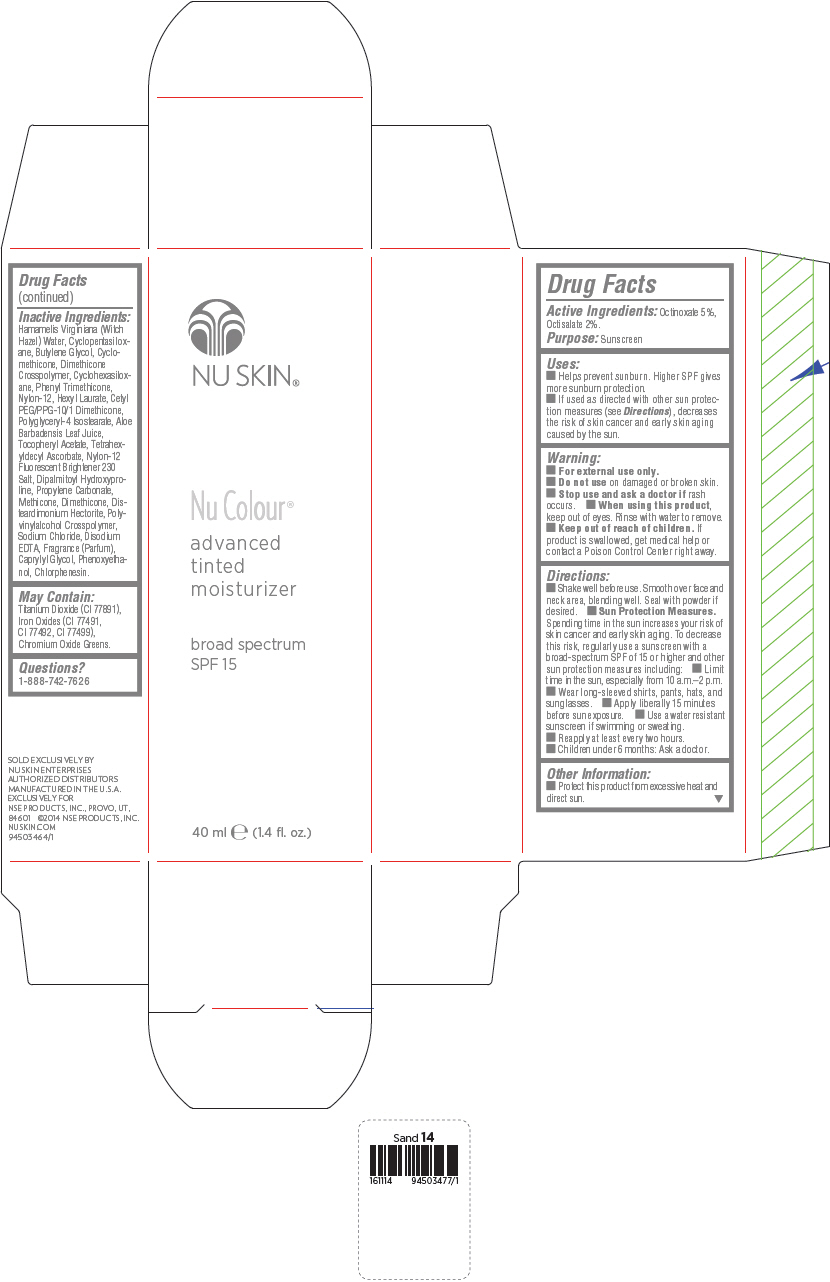 DRUG LABEL: Nu Skin Nu Colour advanced tinted moisturizer broad spectrum SPF 15 - Beige
NDC: 62839-1116 | Form: LOTION
Manufacturer: NSE Products, Inc.
Category: otc | Type: HUMAN OTC DRUG LABEL
Date: 20250103

ACTIVE INGREDIENTS: Octinoxate 50 mg/1 mL; Octisalate 28 mg/1 mL
INACTIVE INGREDIENTS: Hamamelis Virginiana Top Water; Cyclomethicone 5; Butylene Glycol; Titanium Dioxide; Cyclomethicone; Cyclomethicone 6; Phenyl Trimethicone; Nylon-12; Hexyl Laurate; Polyglyceryl-4 Isostearate; Aloe Vera Leaf; .Alpha.-Tocopherol Acetate; Tetrahexyldecyl Ascorbate; Dipalmitoyl Hydroxyproline; Propylene Carbonate; Dimethicone; Disteardimonium Hectorite; Sodium Chloride; Edetate Disodium; Caprylyl Glycol; Phenoxyethanol; Chlorphenesin; Ferric Oxide Red; Ferric Oxide Yellow; Ferrosoferric Oxide

Nu Skin® Nu Colour® advanced tinted moisturizer broad spectrum SPF 15

Drug Facts

Active Ingredients

Octinoxate 5%, Octisalate 2%.

Purpose

Sunscreen

Uses

- Helps prevent sunburn. Higher SPF gives more sunburn protection.
- If used as directed with other sun protection measures (see Directions), decreases the risk of skin cancer and early skin aging caused by the sun.

Warning

- For external use only.

- Do not use on damaged or broken skin.

- Stop use and ask a doctor if rash occurs.

- When using this product, keep out of eyes. Rinse with water to remove.

- Keep out of reach of children. If product is swallowed, get medical help or contact a Poison Control Center right away.

Directions

- Shake well before use. Smooth over face and neck area, blending well. Seal with powder if desired.
- Sun Protection Measures. Spending time in the sun increases your risk of skin cancer and early skin aging. To decrease this risk, regularly use a sunscreen with a broad-spectrum SPF of 15 or higher and other sun protection measures including:
  - Limit time in the sun, especially from 10 a.m.–2 p.m.
  - Wear long-sleeved shirts, pants, hats, and sunglasses.
  - Apply liberally 15 minutes before sun exposure.
  - Use a water resistant sunscreen if swimming or sweating.
- Reapply at least every two hours.
- Children under 6 months: Ask a doctor.

Other Information

- Protect this product from excessive heat and direct sun.

Inactive Ingredients

Hamamelis Virginiana (Witch Hazel) Water, Cyclopentasiloxane, Butylene Glycol, Cyclomethicone, Dimethicone Crosspolymer, Cyclohexasiloxane, Phenyl Trimethicone, Nylon-12, Hexyl Laurate, Cetyl PEG/PPG-10/1 Dimethicone, Polyglyceryl-4 Isostearate, Aloe Barbadensis Leaf Juice, Tocopheryl Acetate, Tetrahexyldecyl Ascorbate, Nylon-12 Fluorescent Brightener 230 Salt, Dipalmitoyl Hydroxyproline, Propylene Carbonate, Methicone, Dimethicone, Disteardimonium Hectorite, Polyvinylalcohol Crosspolymer, Sodium Chloride, Disodium EDTA, Fragrance (Parfum), Caprylyl Glycol, Phenoxyethanol, Chlorphenesin.

May Contain:

Titanium Dioxide (CI 77891), Iron Oxides (CI 77491, CI 77492, CI 77499), Chromium Oxide Greens.

Questions?

1-888-742-7626

PRINCIPAL DISPLAY PANEL - 40 mL Bottle Carton - Beige

NU SKIN®

Nu Colour®

advanced
tinted
moisturizer

broad spectrum
SPF 15

40 ml e (1.4 fl. oz.)

PRINCIPAL DISPLAY PANEL - 40 mL Bottle Carton - Fair

NU SKIN®

Nu Colour®

advanced
tinted
moisturizer

broad spectrum
SPF 15

40 ml e (1.4 fl. oz.)

PRINCIPAL DISPLAY PANEL - 40 mL Bottle Carton - Honey

NU SKIN®

Nu Colour®

advanced
tinted
moisturizer

broad spectrum
SPF 15

40 ml e (1.4 fl. oz.)

PRINCIPAL DISPLAY PANEL - 40 mL Bottle Carton - Medium Beige

NU SKIN®

Nu Colour®

advanced
tinted
moisturizer

broad spectrum
SPF 15

40 ml e (1.4 fl. oz.)

PRINCIPAL DISPLAY PANEL - 40 mL Bottle Carton - Medium Ochre

NU SKIN®

Nu Colour®

advanced
tinted
moisturizer

broad spectrum
SPF 15

40 ml e (1.4 fl. oz.)

PRINCIPAL DISPLAY PANEL - 40 mL Bottle Carton - Natural Beige

NU SKIN®

Nu Colour®

advanced
tinted
moisturizer

broad spectrum
SPF 15

40 ml e (1.4 fl. oz.)

PRINCIPAL DISPLAY PANEL - 40 mL Bottle Carton - Ochre

NU SKIN®

Nu Colour®

advanced
tinted
moisturizer

broad spectrum
SPF 15

40 ml e (1.4 fl. oz.)

PRINCIPAL DISPLAY PANEL - 40 mL Bottle Carton - Pink

NU SKIN®

Nu Colour®

advanced
tinted
moisturizer

broad spectrum
SPF 15

40 ml e (1.4 fl. oz.)

PRINCIPAL DISPLAY PANEL - 40 mL Bottle Carton - Pink Ochre

NU SKIN®

Nu Colour®

advanced
tinted
moisturizer

broad spectrum
SPF 15

40 ml e (1.4 fl. oz.)

PRINCIPAL DISPLAY PANEL - 40 mL Bottle Carton - Sand

NU SKIN®

Nu Colour®

advanced
tinted
moisturizer

broad spectrum
SPF 15

40 ml e (1.4 fl. oz.)